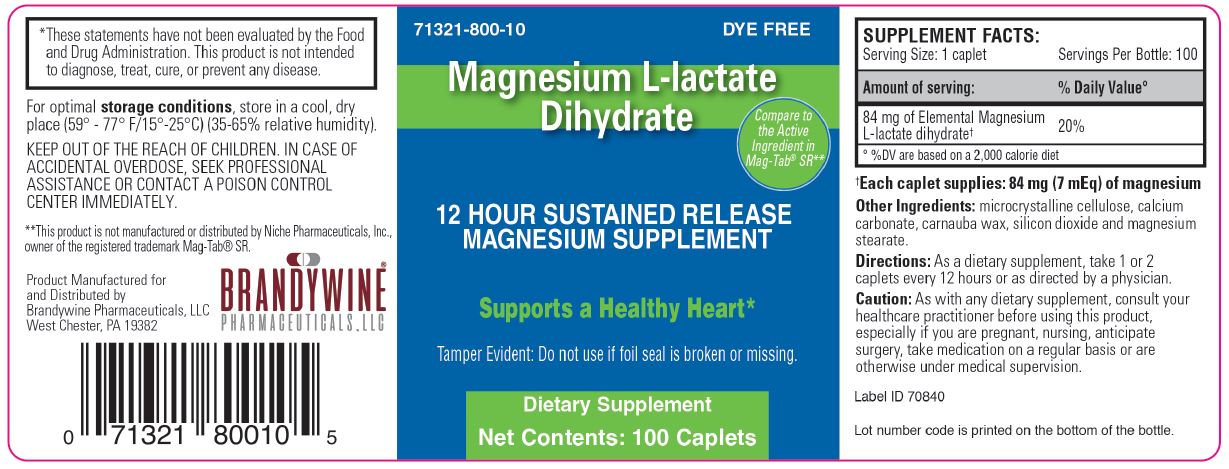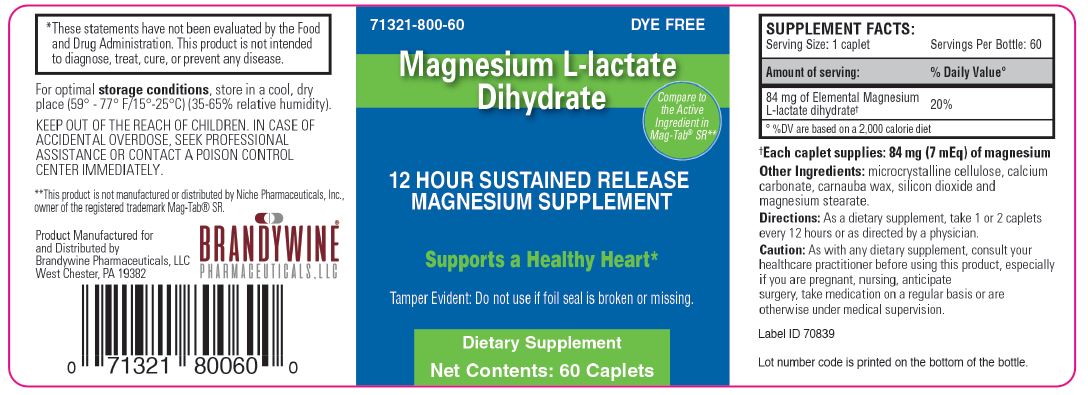 DRUG LABEL: Magnesium L-lactate Dihydrate
NDC: 71321-800 | Form: CAPSULE
Manufacturer: Brandywine Pharmaceuticals, Inc.
Category: other | Type: DIETARY SUPPLEMENT
Date: 20180410

ACTIVE INGREDIENTS: MAGNESIUM LACTATE DIHYDRATE, L- 84 mg/1 1
INACTIVE INGREDIENTS: MICROCRYSTALLINE CELLULOSE; CALCIUM CARBONATE; CARNAUBA WAX; SILICON DIOXIDE; MAGNESIUM STEARATE

Magnesium L-lactate Dihydrate

Statement of Identity

SUPPLEMENT FACTS
Serving Size: 1 caplet | Servings per Bottle: 60
Amount of serving | % Daily Value [% DV are based on a 2,000 calorie diet]
84 mg of Elemental Magnesium L-lactate dihydrate [Each Caplet supplies: 84 mg (7 mEq) of magnesium] | 20

Warning

KEEP OUT OF THE REACH OF CHILDREN. IN CASE OF ACCIDENTAL OVERDOSE, SEEK PROFESSIONAL ASSISTANCE OR CONTACT A POISON CONTROL CENTER IMMEDIATELY

Caution: As with any dietary supplement, consult your healthcare practitioner before using this product, especially if you are pregnant, nursing, anticipate surgery, take medication on a regular basis or are otherwise under medical supervision

Dosage and Administration

Directions: As a dietary supplement, take 1 or 2 caplets every 12 hours or as directed by a physician

Storage

For optimal storage conditions, store in a cool, dry place (59º - 77º F/15º - 25ºC) (35-65% relative humidity)

HEALTH CLAIM

These statements have not been evaluated by the Food and Drug Administration. This product is not intended to diagnose, treat, cure or prevent any disease

PRINCIPAL DISPLAY PANEL - 60 Capsule Bottle Label

NDC: 71321-800-60

Dye Free

Magnesium L-lactate Dihydrate

Compare to the Active Ingredient in Mag-Tab® SR**

12 HOUR SUSTAINED RELEASE MAGNESIUM SUPPLEMENT

Supports a Healthy Heart*

Tamper Evident: Do not use if foil seal is broken or missing.

Dietary Supplement

Net Contents: 60 Caplets

NDC: 71321-800-10

Dye Free

Magnesium L-lactate Dihydrate

Compare to Active Ingredient in Mag-Tab® SR**

12 HOUR SUSTAINED RELEASE MAGNESIUM SUPPLEMENT

Supports a Healthy Heart*

Tamper Evident: Do not use if foil seal is broken or missing.

Dietary Supplement

Net Contents: 100 Caplets